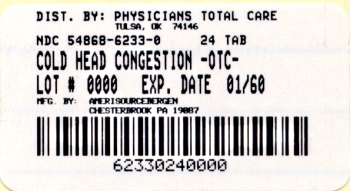 DRUG LABEL: Cold Head Congestion
NDC: 54868-6233 | Form: TABLET, FILM COATED
Manufacturer: Physicians Total Care, Inc.
Category: otc | Type: HUMAN OTC DRUG LABEL
Date: 20111031

ACTIVE INGREDIENTS: ACETAMINOPHEN 325 mg/1 1; DEXTROMETHORPHAN HYDROBROMIDE 10 mg/1 1; PHENYLEPHRINE HYDROCHLORIDE 5 mg/1 1
INACTIVE INGREDIENTS: ACESULFAME POTASSIUM; CARNAUBA WAX; MAGNESIUM STEARATE; CELLULOSE, MICROCRYSTALLINE; POLYETHYLENE GLYCOL; POLYVINYL ALCOHOL; POVIDONE; SILICON DIOXIDE; STEARIC ACID; TALC; TITANIUM DIOXIDE

Cold Head Congestion Drug Facts

Active ingredient (in each caplet)

Acetaminophen 325 mg

Dextromethorphan HBr 10 mg

Phenylephrine HCl 5 mg

Purpose

Pain reliever

Cough suppressant

Nasal decongestant

Uses

- temporarily relieves these common cold symptoms:
- minor aches and pains
- headache
- sore throat
- nasal congestion
- cough
- sinus congestion and pressure
- helps clear nasal passages

Warnings

Liver warning: This product contains acetaminophen. Severe liver damage may occur if you take

- more than 12 caplets in 24 hours, which is the maximum daily amount
- with other drugs containing acetaminophen
- 3 or more alcoholic drinks every day while using this product

Sore throat warning: If sore throat is severe, persists for more than 2 days, is accompanied or followed by fever, headache, rash, nausea, or vomiting, consult a doctor promptly.

Do not use

- with any other drug containing acetaminophen (prescription or nonprescription). If you are not sure whether a drug contains acetaminophen, ask a doctor or pharmacist.
- if you are now taking a prescription monoamine oxidase inhibitor (MAOI) (certain drugs for depression, psychiatric or emotional conditions, or Parkinson’s disease), or for 2 weeks after stopping the MAOI drug. If you do not know if your prescription drug contains an MAOI, ask a doctor or pharmacist before taking this product.

Ask a doctor before use if you have

- liver disease
- heart disease
- high blood pressure
- thyroid disease
- diabetes
- trouble urinating due to an enlarged prostate gland
- cough that lasts or is chronic such as occurs with smoking, asthma or emphysema
- cough that occurs with too much phlegm (mucus)

Ask a doctor or pharmacist before use if you are

taking the blood thinning drug warfarin

When using this product

do not use more than directed

Stop use and ask a doctor if

- you get nervous, dizzy or sleepless
- pain, nasal congestion or cough gets worse or lasts more than 7 days
- fever gets worse or lasts more than 3 days
- redness or swelling is present
- new symptoms occur
- cough comes back or occurs with rash or headache that lasts

These could be signs of a serious condition.

If pregnant or breast-feeding,

ask a health professional before use.

Keep out of reach of children.

In case of overdose, get medical help or contact a Poison Control Center right away. (1-800-222-1222) Quick medical attention is critical for adults as well as for children even if you do not notice any signs or symptoms.

Directions

- do not take more than directed (see Liver warning)

adults and children 12 years and over | - take 2 caplets every 4 hours - do not take more than 12 caplets in 24 hours - swallow whole – do not crush, chew or dissolve
children under 12 years | - do not use this adult product in children under 12 years of age

Other information

- store at 20°-25°C (68°-77°F)

Inactive ingredients

acesulfame potassium, carnauba wax, flavor, magnesium stearate, microcrystalline cellulose, polyethylene glycol, polyvinyl alcohol, povidone, silicon dioxide, sodium starch glycolate, starch, stearic acid, talc, titanium dioxide

Questions or comments?

1-800-719-9260

Principal Display Panel

See New Warnings Information

Compare to active ingredients in Tylenol® Cold Head Congestion Daytime Caplets

Cold

Head Congestion

Pain Reliever, Cough Suppressant, Nasal Decongestant

Contains 3 Medicines:

Headache/Sore Throat – Acetaminophen

Nasal Congestion – Phenylephrine HCl

Coughing – Dextromethorphan HBr

Cool Ice® Instant Cooling Sensation

Daytime

Non-Drowsy

NDC 54868-6233-0

Cold Head Congestion Package Label